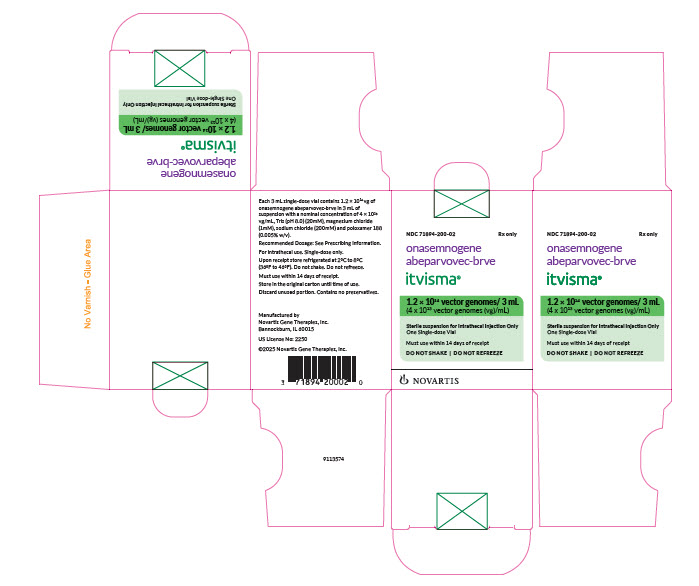 DRUG LABEL: ITVISMA
NDC: 71894-200 | Form: INJECTION, SUSPENSION
Manufacturer: Novartis Gene Therapies, Inc.
Category: prescription | Type: HUMAN PRESCRIPTION DRUG LABEL
Date: 20251124

ACTIVE INGREDIENTS: ONASEMNOGENE ABEPARVOVEC 40000000000000 [arb'U]/1 mL
INACTIVE INGREDIENTS: TROMETHAMINE; MAGNESIUM CHLORIDE; SODIUM CHLORIDE; POLOXAMER 188; WATER

HIGHLIGHTS OF PRESCRIBING INFORMATION

These highlights do not include all the information needed to use ITVISMA safely and effectively. See full prescribing information for ITVISMA.
ITVISMA® (onasemnogene abeparvovec-brve) suspension, for intrathecal injection
Initial U.S. Approval: 2025

WARNING: SERIOUS LIVER INJURY

See full prescribing information for complete boxed warning.

- Acute serious liver injury and elevated aminotransferases can occur with ITVISMA. (5.1)
- Patients with preexisting liver impairment may be at higher risk. (5.1)
- Prior to intrathecal injection, assess liver function by clinical examination and laboratory testing. Administer systemic corticosteroid before and after ITVISMA injection. Continue to monitor liver function for at least 3 months after injection, and at other times as clinically indicated. (2.1, 2.4)

1 INDICATIONS AND USAGE

ITVISMA is an adeno-associated virus (AAV) vector-based gene therapy indicated for the treatment of spinal muscular atrophy (SMA) in adult and pediatric patients 2 years of age and older with confirmed mutation in SMN1 gene. (1)

2 DOSAGE AND ADMINISTRATION

For single-dose intrathecal injection only. (2)

- The recommended dose of ITVISMA is 1.2 × 10^14 vector genomes (vg). (2.2)
- Administer ITVISMA as an intrathecal bolus injection over approximately 1 to 2 minutes. (2.4)
- Postpone ITVISMA in patients with infections until the infection has resolved and the patient is clinically stable. (2.1)
- Starting one day prior to ITVISMA injection, administer systemic corticosteroids equivalent to oral prednisolone at 1 mg/kg of body weight per day for a total of 30 days. At the end of the 30-day period, check liver function by clinical examination and by laboratory testing. For patients with unremarkable findings, taper the corticosteroid dose gradually over the next 28 days. If liver function abnormalities persist, continue systemic corticosteroids (equivalent to oral prednisolone at 1 mg/kg/day) until findings become unremarkable, and then taper the corticosteroid dose gradually over the next 28 days or longer if needed. Do not stop systemic corticosteroids abruptly. (2.2)
- If at any time patients do not respond adequately to the equivalent of 1 mg/kg/day oral prednisolone, based on the patient’s clinical course, prompt consultation with a gastroenterologist or hepatologist and adjustment to the recommended corticosteroid regimen may be considered. (2.2)

3 DOSAGE FORMS AND STRENGTHS

Each single-dose vial contains 1.2 × 10^14 vg of onasemnogene abeparvovec in 3 mL of suspension. ITVISMA has a nominal concentration of 4 × 10^13 vg/mL, and each vial contains an extractable volume of not less than 3 mL. (3)

4 CONTRAINDICATIONS

None. (4)

5 WARNINGS AND PRECAUTIONS

- Hepatotoxicity: Prior to ITVISMA injection, assess liver function of patients by clinical examination and laboratory testing. Continue to monitor liver function for at least 3 months after injection, and at other times as clinically indicated. (2.1, 2.4, 5.1)
- Thrombocytopenia: Monitor platelet counts before ITVISMA injection, and at least weekly for the first month and as clinically indicated until platelet counts return to baseline. (2.1, 2.4, 5.2)
- Peripheral Sensory Neuropathy: Consider complete neurologic evaluation and other testing and/or symptom management based on the patient's clinical presentation. (5.3)
- Thrombotic Microangiopathy (TMA): Prompt attention to signs and symptoms of TMA is advised, as TMA can result in life-threatening or fatal outcomes. If clinical signs, symptoms and/or laboratory findings occur, consult a hematologist and/or nephrologist immediately to manage as clinically indicated. (5.4)
- Elevated Cardiac Troponin I: Increases in cardiac troponin I have occurred following ITVISMA injection. Consider cardiac evaluation after ITVISMA administration and consult a cardiologist as needed. (5.5)
- AAV Vector Integration and Risk of Tumorigenicity: There is a theoretical risk of tumorigenicity due to integration of AAV vector DNA into the genome. Report cases of tumors in patients who received ITVISMA, to Novartis Gene Therapies, Inc. (5.6)

6 ADVERSE REACTIONS

The most common adverse reactions that occurred in at least 10% of patients were upper respiratory tract infection, upper gastrointestinal symptoms, pyrexia, and headache. (6)

To report SUSPECTED ADVERSE REACTIONS, contact Novartis Gene Therapies at 1-833-828-3947 or FDA at 1-800-FDA-1088 or www.fda.gov/medwatch.

7 DRUG INTERACTIONS

Adjust patient’s vaccination schedule to accommodate concomitant corticosteroid administration prior to and following ITVISMA injection. (7)

FULL PRESCRIBING INFORMATION

WARNING: SERIOUS LIVER INJURY

- Acute serious liver injury and elevated aminotransferases can occur with ITVISMA. [see Warnings and Precautions (5.1)]
- Patients with preexisting liver impairment may be at higher risk. [see Warnings and Precautions (5.1)]
- Prior to intrathecal injection, assess liver function by clinical examination and laboratory testing. Administer systemic corticosteroid before and after ITVISMA injection. Continue to monitor liver function for at least 3 months after injection, and at other times as clinically indicated. [see Dosage and Administration (2.1, 2.4)].

1 INDICATIONS AND USAGE

ITVISMA is indicated for the treatment of spinal muscular atrophy (SMA) in adult and pediatric patients 2 years of age and older with confirmed mutation in survival motor neuron 1 (SMN1) gene.

2 DOSAGE AND ADMINISTRATION

2.1 Critical Dosing Information

For single-dose intrathecal injection only.

- Patients previously treated with ZOLGENSMA (onasemnogene abeparvovec-xioi) should not be treated with ITVISMA [see Clinical Pharmacology (12.1)].
- ITVISMA should only be administered intrathecally using a lumbar puncture by healthcare professionals (e.g., interventional radiologist or neurologist) experienced in performing lumbar punctures.
- Prior to ITVISMA injection:
  - Due to the increased risk of serious systemic immune response, administer ITVISMA to patients who are clinically stable in their overall baseline health status (e.g., hydration and nutritional status, absence of infection, respiratory status) prior to administration. Postpone ITVISMA in patients with active or recent infections, until the infection has resolved, and the patient is clinically stable. Clinical signs or symptoms of infection should not be evident at the time of ITVISMA injection.
  - Assess vaccination status. Vaccination status should be up-to-date prior to ITVISMA administration. Recommend seasonal prophylaxis against respiratory syncytial virus (RSV).
  - Assess liver function (clinical examination and laboratory testing including aspartate aminotransferase (AST), alanine aminotransferase (ALT), albumin, prothrombin time, partial thromboplastin time (PTT), international normalized ratio (INR), and total bilirubin) [see Warnings and Precautions (5.1), Use in Specific Populations (8.6)].
  - Obtain creatinine and complete blood count (including hemoglobin and platelet count) [see Warnings and Precautions (5.2, 5.4)].
  - Perform baseline testing for the presence of anti-AAV9 antibodies.
- One day prior to ITVISMA injection, begin administration of systemic corticosteroids equivalent to oral prednisolone at 1 mg per kg of body weight per day (mg/kg/day) for a total of 30 days. Do not stop systemic corticosteroids abruptly. After the 30-day period, taper prednisolone (or equivalent) as needed according to the clinical status and liver function testing [see Warnings and Precautions (5.1, 5.2)]. See Table 1 for the recommended corticosteroid regimen.
- Do not re-administer ITVISMA.

2.2 Dose

The recommended dose of ITVISMA is 1.2 × 10^14 vector genomes (vg).

Table 1 includes the recommended corticosteroid regimen prior to and following ITVISMA injection.

If at any time patients do not respond adequately to the equivalent of 1 mg/kg/day oral prednisolone, based on the patient’s clinical course, obtain prompt consultation with a gastroenterologist or hepatologist and consider adjustment to the recommended corticosteroid regimen, including increased dose, longer duration or prolongation of corticosteroid taper [see Warnings and Precautions (5.1)]. If oral corticosteroid therapy is not tolerated or not effective, consider intravenous corticosteroids, as clinically indicated.

Table 1: Recommended Corticosteroid Regimen Pre- and Post- ITVISMA Injection
Pre-Injection | -
24 hours prior to ITVISMA injection | Oral prednisolone 1 mg/kg/day (or equivalent)
Post-Injection | -
30 days (including the day of ITVISMA administration) | Oral prednisolone 1 mg/kg/day (or equivalent)
Followed by 28 days: For patients with unremarkable findings (normal clinical exam, total bilirubin, and ALT and AST levels below 2 × ULN) or For patients with liver function abnormalities at the end of the 30 day period: continue until the AST and ALT values are both below 2 × ULN and all other assessments return to normal range, and then taper the corticosteroid dose over the next 28 days or longer if needed. | Systemic corticosteroids should be tapered gradually Taper prednisolone (or equivalent) Systemic corticosteroids (equivalent to oral prednisolone 1 mg/kg/day) Systemic corticosteroids should be tapered gradually

2.3 Preparation

Required supplies and materials (not supplied)

- Needle for withdrawal
- Syringe
- Syringe cap
- Spinal needle

The supplies and materials compatible with ITVISMA are listed in Table 2. Device components must be indicated for intrathecal or neuraxial use. Ensure all device components use the same connector type. Incompatible device connections may result in dose loss during administration.

Table 2: Component Materials Compatible With ITVISMA
Component | Material of Construction
18G to 19G Needle for withdrawal, maximum 1.5” long | Stainless steel
5mL to 10mL Syringea | Polypropylene
Syringe capa | Polypropylene or Polyethylene or Methacrylate-Acrylonitrile-Butadiene-Styrene
22G to 27G Spinal needle, maximum 150mm long | Stainless steel
aNot to be manufactured with Polyvinylchloride (PVC), Bisphenol-A (BPA), Bis(2- ethylhexyl) phthalate (DEHP) or Latex

Vial Preparation:

- ITVISMA should be prepared aseptically.
- Thaw ITVISMA in the refrigerator for approximately 4 hours, or at room temperature for approximately 1 hour. If thawed in the refrigerator, remove ITVISMA from refrigerator on day of dosing.
- Do not use ITVISMA unless thawed.
- Prior to intrathecal injection, ITVISMA should be brought to room temperature.
- When thawed, ITVISMA is a clear to slightly opaque, colorless to faint white liquid, free of particles. After withdrawal of ITVISMA from the vial, a visual inspection is required. DO NOT use if particulates, cloudiness, or discoloration are visible.
- DO NOT SHAKE.
- Immediately prior to dosing, draw the content from the vial into the syringe, remove air from syringe, confirm the dose volume of 3 mL in the syringe, cap syringe and deliver to patient injection location.
- Once dose is drawn into the syringe, it may be held in the refrigerator at 2°C to 8°C (36°F to 46°F) for up to 24 hours, including a 5-hour maximum time out-of-refrigeration allowance within the 24-hour period. Discard the vector-containing syringe if not injected within this time period.
- DO NOT REFREEZE.

Procedural Preparation Instructions:

- Consider sedation if indicated by the patient’s clinical status.
- Consider imaging techniques to guide intrathecal injection of ITVISMA.
- Evaluate patient prior to and after intrathecal injection for conditions that may contraindicate lumbar puncture or increase procedural risk to prevent serious complications.

2.4 Administration

Intrathecal Injection Instructions:

- Prior to administration, remove 3 mL of cerebrospinal fluid (CSF) using a lumbar puncture needle to create space for injection volume.
- Administer ITVISMA as an intrathecal bolus injection over approximately 1 to 2 minutes through the lumbar puncture needle.
- Place patient in Trendelenburg position (head down at 30 degrees for 15 minutes). Adjust patient positioning and duration based on the patient’s clinical status to enhance distribution.
- Follow standard post-lumbar puncture care protocols.

Monitoring Following ITVISMA Injection:

- Liver function (AST, ALT, total bilirubin) weekly for the month after ITVISMA injection and during the corticosteroid taper period (over the next 28 days or longer if needed). If the patient is clinically stable with unremarkable findings (normal clinical exam, total bilirubin, and ALT and AST levels below 2 × ULN) at the end of the corticosteroid taper period, continue to monitor liver function every other week for another month [see Warnings and Precautions (5.1)].
- Platelet counts weekly for the first month and as clinically indicated until platelet counts return to baseline [see Warnings and Precautions (5.2)].

3 DOSAGE FORMS AND STRENGTHS

ITVISMA is a clear to slightly opaque, colorless to faint white suspension for intrathecal injection.

Each single-dose vial contains 1.2 × 10^14 vg of onasemnogene abeparvovec in 3 mL of suspension.

ITVISMA has a nominal concentration of 4 × 10^13 vg/mL, and each vial contains an extractable volume of not less than 3 mL.

4 CONTRAINDICATIONS

None.

5 WARNINGS AND PRECAUTIONS

5.1 Hepatotoxicity

Hepatotoxicity, with elevated ALT and/or AST levels, has occurred with ITVISMA [see Adverse Reactions (6.1)]. Patients with preexisting hepatic impairment or acute hepatic viral infection may be at higher risk of liver injury. In order to mitigate potential aminotransferase elevations, administer systemic corticosteroid before and after ITVISMA injection. Immune-mediated hepatotoxicity may require adjustment of the corticosteroid treatment regimen, including longer duration, increased dose, or prolongation of the corticosteroid taper [see Dosage and Administration (2.2)].

Prior to ITVISMA injection, assess liver function by clinical examination and laboratory testing. Continue to monitor liver function for at least 3 months after ITVISMA administration, and at other times as clinically indicated. Monitor AST, ALT and total bilirubin weekly for the month after ITVISMA administration and during the corticosteroid taper period. If the patient is clinically stable with unremarkable findings at the end of the corticosteroid taper period, continue to monitor liver function every other week for another month. Tapering of systemic corticosteroids should not be considered until AST/ALT levels are less than 2 × ULN [see Dosage and Administration (2.1, 2.4)].

Monitor patients with worsening liver function test results and/or signs or symptoms of acute illness (e.g., vomiting, deterioration in health). In case hepatic injury is suspected, further testing is recommended (e.g., albumin, prothrombin time, partial thromboplastin time (PTT) and international normalized ratio (INR)). Promptly consult with a gastroenterologist or hepatologist, as necessary.

5.2 Thrombocytopenia

Transient decreases in platelet counts were observed within the first week after ITVISMA administration [see Adverse Reactions (6.1)]. The platelets counts are expected to return to baseline two weeks following ITVISMA injection.

Monitor platelet counts before ITVISMA injection and on a regular basis afterwards (at least weekly for the first month and as clinically indicated until platelet counts return to baseline) [see Dosage and Administration (2.1, 2.4)].

5.3 Peripheral Sensory Neuropathy

Peripheral sensory neuropathy has occurred with ITVISMA administration [see Adverse Reactions (6.1)]. Signs and symptoms may include numbness, tingling, prickling, or pain in the arms, hands, legs and/or feet, with onset seen at approximately three weeks post-injection in clinical studies.

Consider complete neurologic evaluation and other testing and/or symptom management based on the patient's clinical presentation. Inform patients and caregivers about the signs and symptoms of peripheral sensory neuropathy, and advise patients and caregivers to notify their physician promptly if such symptoms occur.

5.4 Thrombotic Microangiopathy

Thrombotic microangiopathy (TMA) may occur with ITVISMA administration. TMA is characterized by thrombocytopenia, microangiopathic hemolytic anemia, and acute kidney injury. Concurrent immune system activation (e.g., infections, vaccinations) may be a contributing factor.

Prompt attention to signs and symptoms of TMA is advised, as TMA can result in life-threatening or fatal outcomes.

Monitor platelet counts on a regular basis following ITVISMA injection [see Warnings and Precautions (5.2)], as well as signs and symptoms of TMA, such as hypertension, bruising easily, seizures, or decreased urine output. In case these signs and symptoms occur in the presence of thrombocytopenia, further diagnostic evaluation for hemolytic anemia and renal dysfunction should be promptly undertaken. If clinical signs, symptoms and/or laboratory findings consistent with TMA occur, consult a hematologist and/or nephrologist immediately to manage TMA as clinically indicated.

5.5 Elevated Cardiac Troponin I

Increases in cardiac troponin I levels have occurred following ITVISMA administration without clinical sequelae [see Adverse Reactions (6.1)]. Cardiac toxicity was observed in animal studies [see Nonclinical Toxicology (13.2)]. Consider cardiac evaluation after ITVISMA administration and consult a cardiologist as needed.

5.6 AAV Vector Integration and Risk of Tumorigenicity

There is a theoretical risk of tumorigenicity due to integration of AAV vector DNA into the genome.

ITVISMA is composed of a recombinant, non-replicating AAV9 vector whose DNA persists largely in episomal form. Random integration of recombinant AAV-vector DNA into human DNA has been reported with AAV gene therapies. The clinical relevance of individual integration events is unknown, but it is acknowledged that individual integration events could potentially contribute to a risk of tumorigenicity. If a tumor develops in a patient receiving ITVISMA, health care providers should contact and report the tumor to Novartis Gene Therapies, Inc. at 1-833-828-3947.

6 ADVERSE REACTIONS

6.1 Clinical Trials Experience

Because clinical trials are conducted under widely varying conditions, adverse reaction rates observed in the clinical trials of a drug cannot be directly compared to rates in the clinical trials of another product and may not reflect the rates observed in practice.

The safety data described in this section reflects exposure of ITVISMA in two clinical studies, Study 1, a randomized, sham-controlled study which evaluated the safety of ITVISMA in 126 patients with spinal muscular atrophy (SMA) and Study 2, an open-label-single arm study which evaluated safety of ITVISMA in 27 patients with SMA who were previously treated with nusinersen (at least 4 months washout) or risdiplam (at least 15 days washout). In Study 1, a total of 75 patients received a single intrathecal injection of ITVISMA at a fixed dose of 1.2 x 10^14 vg and 51 patients underwent a sham-procedure [see Clinical Studies (14)]. In Study 2, a total of 27 patients received a single intrathecal injection of ITVISMA at a fixed dose of 1.2 x 10^14 vg. The patients were followed for a duration of 52 weeks for both studies.

In Study 1, serious adverse reactions were reported in four patients (5%) including elevated liver enzymes (n=1), sensory disturbance (n=2), and vomiting (n=1).

The most frequent adverse reactions occurring in ≥ 2% of patients in Study 1 are summarized in Table 3 below.

Table 3: Adverse Reactions Occurring in ≥2% of Patients or with higher frequency in ITVISMA-treated Patients compared to Sham group in Study 1
Adverse reactions | ITVISMA | Sham
 | (N = 75), n (%) | (N = 51), n (%)
Upper respiratory tract infection* | 31 (41) | 15 (29)
Pyrexia | 19 (25) | 12 (24)
Upper gastrointestinal symptoms* | 20 (27) | 8 (16)
Hepatic enzyme increased* | 6 (8)a | 5 (10)
Headache | 8 (11) | 2 (4)
Dizziness | 4 (5) | 1 (2)
Pain in extremity | 3 (4) | 1 (2)
Thrombocytopenia* | 3 (4) | 0
Sensory disturbance* | 2 (3)b | 1 (2)c
*Is a composite that includes multiple related terms
a)Two patients had ALT elevations of 20 times the upper limit of normal (ULN)
b)Signs and symptoms that may be suggestive of dorsal root ganglion (DRG) toxicity occurred within 3 weeks of ITVISMA injection and stabilized but remained unresolved at the end of study period.
c)Occurred 154 days after the sham procedure and resolved after 15 days without intervention.

The safety evaluated in Study 2 did not identify any additional safety events with ITVISMA administration.

6.2 Postmarketing Experience

The following adverse reactions have been identified during post-approval use of ZOLGENSMA, a similar product containing the same active ingredient (onasemnogene abeparvovec) administered intravenously. Because these reactions are reported voluntarily, it is not always possible to reliably estimate their frequency or establish a causal relationship to drug exposure.

Blood and Lymphatic System Disorders: thrombotic microangiopathy

Hepatobiliary Disorders: acute liver failure (fatal and non-fatal), acute liver injury

General Disorders and Administration Site Conditions: pyrexia, infusion-related reactions

Investigations: troponin increased

7 DRUG INTERACTIONS

Adjust patient’s vaccination schedule to accommodate concomitant corticosteroid administration prior to and following ITVISMA injection [see Dosage and Administration (2.1)]. Certain vaccines, such as measles, mumps, and rubella (MMR) and varicella, are contraindicated for patients on a substantially immunosuppressive steroid dose (i.e., ≥ 2 weeks of daily receipt of 20 mg or 2 mg/kg body weight of prednisone or equivalent).

8 USE IN SPECIFIC POPULATIONS

8.1 Pregnancy

Risk Summary

There are no clinical studies in pregnant women to inform a product-associated risk. There are no available data in animal embryo-fetal development studies with ITVISMA. It is not known whether ITVISMA has the potential to be transferred to the fetus. Therefore, women who are pregnant or desire to become pregnant should only be treated with ITVISMA after a thorough benefit-risk evaluation.

In the United States general population, the estimated background risk of major birth defects and miscarriage in clinically recognized pregnancies is 2% to 4% and 15% to 20%, respectively.

8.2 Lactation

Risk Summary

There is no information available on the presence of ITVISMA in human milk, the effects on the breastfed infant or the effects on milk production. The developmental and health benefits of breastfeeding should be considered along with the mother’s clinical need for ITVISMA and any potential adverse effects on the breastfed child from ITVISMA or from the underlying maternal condition.

8.3 Females and Males of Reproductive Potential

Pregnancy Testing

The pregnancy status of females of reproductive potential should be verified prior to treatment with ITVISMA [see Use in Specific Populations (8.1)].

Contraception

Females of reproductive potential should use effective contraception (methods that result in less than 1% pregnancy rates) and should refrain from egg donation for 6 months following ITVISMA administration. Men capable of fathering a child should use a barrier method of contraception and should refrain from sperm donation for 3 months following ITVISMA administration.

Infertility

There is no data on the effect of ITVISMA on human fertility. In animal fertility studies, onasemnogene abeparvovec did not impact fertility in male and female mice at a dose of 1.1 × 10^14 vg/kg administered intravenously [see Nonclinical Toxicology (13.1)].

8.4 Pediatric Use

The safety and efficacy of ITVISMA have been established in pediatric patients 2 years of age and older. The use of ITVISMA was supported by data from one clinical study (Study 1) which enrolled 126 pediatric patients 2 years of age and older [see Adverse Reaction (6) and Clinical Studies (14)].

The safety and effectiveness of ITVISMA have not been established in pediatric patients younger than 2 years of age.

8.6 Hepatic Impairment

Patients with preexisting hepatic impairment or acute hepatic viral infection may be at higher risk of liver injury. ITVISMA therapy should be carefully considered in patients with liver impairment [see Warnings and Precautions (5.1)].

11 DESCRIPTION

ITVISMA (onasemnogene abeparvovec-brve) is a suspension of an adeno-associated viral vector-based gene therapy for intrathecal injection. It is a recombinant self-complementary AAV9 containing a transgene encoding the human survival motor neuron (SMN) protein, under the control of a cytomegalovirus enhancer/chickenβactin hybrid promoter.

ITVISMA has a nominal concentration of 4 × 10^13 vg/mL. Each vial contains an extractable volume of not less than 3 mL and the excipients 20 mM Tris (pH 8.0), 1 mM magnesium chloride (MgCl2), 200 mM sodium chloride (NaCl) and 0.005% poloxamer 188. ITVISMA is packaged as a sterile suspension and contains no preservative.

12 CLINICAL PHARMACOLOGY

12.1 Mechanism of Action

ITVISMA is a non-replicating recombinant AAV vector that utilizes AAV9 capsid to deliver a functional copy of human survival motor neuron 1 gene (SMN1). The transgene DNA persists largely in episomal form in the nucleus of transduced cells. Expression of the transgene is driven by a constitutive promoter (cytomegalovirus enhanced chicken β actin hybrid), resulting in continuous and sustained SMN expression. SMA is caused by a bi-allelic mutation in the SMN1 gene, which results in insufficient SMN protein expression. By providing an alternative source of SMN protein expression in motor neurons, it is expected to promote the survival and function of transduced motor neurons.

12.2 Pharmacodynamics

There are no clinically relevant pharmacodynamics data for ITVISMA.

12.3 Pharmacokinetics

Nonclinical Biodistribution

Intrathecal (IT) administration of onasemnogene abeparvovec to non-human primates (NHPs) at dose levels of 1.2 × 10^13 (equivalent to the clinical therapeutic dose), 3.0 × 10^13, or 6.0 × 10^13 vector genomes (vg)/animal, resulted in biodistribution of the vector to all the CNS and peripheral tissues assessed. Vector DNA concentrations were highest in the liver, followed by the dorsal root ganglia (DRG) and spinal cord, with the lowest concentrations detected in the gonads. Vector DNA concentrations in the spinal cord tended to remain stable between 6-weeks and 12-months post-administration at all dose levels assessed.

Intrathecal or intra-cisterna magna administration of a tool scAAV9CB-GFP vector to adult NHPs resulted in the detection of vector DNA in the oocytes and ovarian stromal cells of females administered 1.0 × 10^13 and 3.0 × 10^13 vg/animal at 28-days post-administration of the product. In mice, IV, or intracerebroventricular (ICV) administration of onasemnogene abeparvovec resulted in no detection of vector DNA in the germline cells of males and females at 24 weeks post-administration.

In non-human primates, high pre-existing serum anti-AAV9 antibody titers (corresponding to human titer values of up to approximately 1:25000) were not shown to affect scAAV9 vector (utilized in onasemnogene abeparvovec) DNA distribution in the spinal cord following intrathecal administration.

Clinical Vector Shedding

ITVISMA vector shedding studies, which assess the amount of vector DNA eliminated from the body through saliva, urine, feces and nasal secretions were performed following intrathecal administration in 134 patients.

Vector DNA was detectable in shedding samples in 134 patients following intrathecal injection of ITVISMA. Shedding of onasemnogene abeparvovec DNA was primarily via feces. Peak shedding in participants was observed within 10-, 3-, 2-, and 8 days post-dose for stool, urine, saliva and nasal secretion, respectively. The majority of the vector DNA (> 90%) is excreted within 2 weeks after dose administration.

12.6 Immunogenicity

The observed incidence of anti-drug antibodies is highly dependent on the sensitivity and specificity of the assay. Differences in assay methods preclude meaningful comparisons of the incidence of anti-drug antibodies in the studies described below with the incidence of anti-drug antibodies in other studies, including those of ITVISMA or of other AAV gene therapy products.

In Study 1 and Study 2, anti-AAV9 antibody titers were evaluated in 102 patients following a single intrathecal injection of ITVISMA. In these studies, patients were required to have baseline anti-AAV9 antibody titers ≤ 1:50.

Increases from baseline in anti-AAV9 antibody titers were reported in all patients with a median anti-AAV9 antibody titers of ≥ 1:819,200 at 12 months following ITVISMA injection in both studies.

During the 12-month period following ITVISMA injection in Study 1 and Study 2, positive anti-SMN antibodies were observed in 5/75 (6.7%) and 2/27 (7.4%) of ITVISMA-treated patients, respectively. There was no identified clinical effect of anti-SMN and anti-AAV9 antibodies on safety or efficacy of ITVISMA over the follow-up period of 12 months post-dose.

13 NONCLINICAL TOXICOLOGY

13.1 Carcinogenesis, Mutagenesis, Impairment of Fertility

No animal studies have been performed to evaluate the effects of onasemnogene abeparvovec on carcinogenesis or mutagenesis.

In fertility and early embryonic development studies conducted in male and female mice, intravenous administration of onasemnogene abeparvovec at dose levels up to 1.1 × 10^14 vector genomes (vg)/kg body weight had no effect on fertility, fecundity, or mating indices. There was no evidence of germ cell transduction or germline transmission.

13.2 Animal Toxicology and/or Pharmacology

A single intrathecal (IT) dose of onasemnogene abeparvovec was administered at three dose levels: 1.20 × 10^13 vg/animal (equivalent to the clinical therapeutic dose), 3.0 × 10^13 vg/animal, and 6.0 × 10^13 vg/animal. At 6 weeks post-administration, all dose levels resulted in acute, minimal to moderate mononuclear cell inflammation and neuronal degeneration across multiple anatomical sites, including the cerebrum, cerebellar white matter, brain stem, dorsal root ganglia (DRG), and various nerve structures (trigeminal, dorsal spinal, spinal, and peripheral nerves). Additionally, axonal degeneration and/or gliosis was observed in the spinal cord. These findings partially or fully resolved by 12 months post-administration and had no correlative clinical observations. Elevated liver enzyme levels (aspartate and alanine amino transferase) and single cell necrosis of hepatocytes were observed in select NHPs at 6 weeks post-administration but resolved by 12 months post-administration.

14 CLINICAL STUDIES

The efficacy of ITVISMA was evaluated in a randomized, double-blind, sham-controlled study (Study 1; NCT05089656). The study enrolled patients with spinal muscular atrophy (SMA) who were treatment-naive, and able to sit but never able to walk independently. Patients with elevated (reference to > 1:50) baseline serum anti-AAV9 antibody titer were excluded.

A total of 136 patients were randomized in 3:2 ratio to receive either ITVISMA at a dose of 1.2 x 10^14 vg by single lumbar intrathecal injection or sham procedure. Randomization was stratified by age and pre-treatment Hammersmith Functional Motor Scale – Expanded (HFMSE) score at screening. A total of 126 patients received the assigned treatment and were included in the efficacy evaluation.

The demographic characteristics of the population were as follows: the mean age was 6 years (range 2 to 17 years), 62 patients (49%) were male, 74 patients (59%) were Asian, 14 patients (11%) were White, 9 patients (7%) were Black or African American, and 7 patients (6%) were American Indian or Alaska Native, 22 patients (18%) were of “unknown” race. One hundred and twenty-two patients (97%) had confirmed biallelic deletion (0 copies) of the SMN1 gene, while 4 patients (3%) had 1 copy. Patients' highest motor function ever achieved were as follows: 66 patients (52%) sitting without support, 33 patients (26%) standing with assistance, 24 patients (19%) walking with assistance, and 3 patients (2%) standing independently. At baseline, the mean HFMSE total score was 17.97 (range 1.0 - 41.0) and 18.17 (range 2.0 - 42.5) in the ITVISMA-treated group and sham group, respectively.

The primary endpoint was the change from baseline in HFMSE total score at the end of follow-up, defined as the average of the Week 48 and Week 52 assessment, in ITVISMA compared to sham. The HFMSE evaluates motor function in patients with SMA who have limited ambulation, comprising of 33 graded items that assess various motor skills ranging from sitting to using the stairs. Each item is scored from 0-2, with a maximum total score of 66. Higher scores indicate better motor function.

The efficacy results from Study 1 are summarized in Table 4 below.

Table 4: Efficacy Results from the Study 1 (n=126)
Endpoint | ITVISMA (N = 75) | Sham (N = 51) | Treatment Difference ITVISMA-Sham (95% CI) | p-value
Mean change from baseline in HFMSE total score at the end of follow-up^(1, 2, 3) | 2.39 (0.439)^4 | 0.51 (0.532)^4 | 1.88 (0.51 – 3.25) | 0.0074
CI = confidence interval
^1Assessed using the Full Analysis Set (FAS) population, which included all participants who were dosed with ITVISMA (n=75) or who underwent sham procedure (n=51). The follow-up period was defined as the average of the Week 48 and Week 52 assessment.
^2Least squares (LS) mean.
^3Estimated using a linear mixed model repeated measures (MMRM) model with the observed change from Baseline in HFMSE total score at all post-baseline visits as the dependent variable. The fixed effects included treatment, visit, treatment by visit interaction, the strata, and the baseline HFMSE total score as covariate. An unstructured covariance matrix was used.
^4Standard error of the mean (SEM)

16 HOW SUPPLIED/STORAGE AND HANDLING

16.1 How Supplied

ITVISMA is supplied as a sterile, preservative-free, clear to slightly opaque, colorless to faint white suspension for intrathecal injection. ITVISMA contains 4 × 10^13 vg per mL.

Each carton of ITVISMA contains a single-dose vial with an extractable volume of not less than 3 mL, containing 1.2 × 10^14 vg.

Carton containing one 1.2 × 10^14 vg/3 mL (4 × 10^13 vg/mL) single-dose vial.

Container (vial): NDC Number 71894-200-01

Package (carton): NDC Number 71894-200-02

16.2 Storage and Handling

- Product is shipped and delivered frozen (≤ -60°C [-76°F]) in a single-dose clear vial.
- Upon receipt, immediately place the carton in a refrigerator at 2°C to 8°C (36°F to 46°F).
- ITVISMA is stable for 14 days from receipt when stored at 2°C to 8°C (36°F to 46°F).
- DO NOT REFREEZE.
- Must use within 14 days of receipt.

17 PATIENT COUNSELING INFORMATION

Hepatotoxicity

Inform patients and caregivers that ITVISMA could increase liver enzyme levels. Inform patients and caregivers that patients will receive an oral corticosteroid medication before and after ITVISMA injection, and will undergo regular blood tests to monitor liver function. Advise patients and caregivers to contact their healthcare provider immediately if the patient’s skin and/or whites of the eyes appear yellowish, if the patient misses a dose of corticosteroid or vomits it up, or if the patient experiences a decrease in alertness [see Warnings and Precautions (5.1)].

Vaccination Before and After ITVISMA Injection

Advise patients and caregivers to consult with their healthcare provider to determine if adjustments to the patient’s vaccination schedule are necessary during corticosteroid use. Inform patients and caregivers that where feasible, the vaccination schedule should be adjusted appropriately to accommodate treatment with corticosteroid. Prophylaxis against influenza and RSV is recommended and vaccination status should be up-to-date prior to ITVISMA administration. Please consult your health care provider [see Dosage and Administration (2.1), Drug Interactions (7)].

Concurrent Infections

Patients and caregivers should be aware that an infection (e.g., cold, flu, gastroenteritis, otitis media, bronchiolitis, etc.) before or after ITVISMA injection could lead to more serious complications. Patients, caregivers and close contacts of patients should follow infection prevention practices (e.g., hand hygiene, coughing/sneezing etiquette, limiting potential contacts). Advise patients and caregivers of the signs of a possible infection, such as coughing, wheezing, sneezing, runny nose, sore throat, or fever. Patients and caregivers should contact their healthcare provider immediately if the patient experiences any symptoms suggestive of infection before or after ITVISMA injection [see Dosage and Administration (2.1)].

Thrombocytopenia

Inform patients and caregivers that ITVISMA could decrease blood platelet count and increase the risk of bruising or bleeding. Inform patients and caregivers that decreases in platelet counts were observed within the first week after ITVISMA injection. Advise patients and caregivers to seek medical attention if the patient experiences unexpected bruising or bleeding [see Warnings and Precautions (5.2)].

Peripheral Sensory Neuropathy

Inform patients and caregivers that peripheral sensory neuropathy has occurred with ITVISMA administration. Advise patients and caregivers to contact their healthcare provider promptly if the patient experiences numbness, tingling, prickling, or pain in the arms, hands, legs and/or feet [see Warnings and Precautions (5.3)].

Thrombotic Microangiopathy

Inform patients and/or caregivers that decreased blood platelet and red blood cell counts, acute kidney injury, and increased bruising or bleeding, which may be indicative of TMA, can occur. Advise patients and/or caregivers to seek immediate medical attention if the patient experiences unexpected bruising or bleeding, seizures, or decreased urine output [see Warnings and Precautions (5.4)].

AAV Vector Integration and Risk of Tumorigenicity

Inform patients and/or caregivers that there is a theoretical risk of tumorigenicity with AAV therapies such as ITVISMA. Advise patients and/or caregivers to contact their healthcare provider and Novartis Gene Therapies, Inc. (1-833-828-3947) if the patient who received ITVISMA develops a tumor [see Warnings and Precautions (5.6)].

Contraception and Egg/Sperm Donation

Advise women of childbearing potential to use an effective method of contraception and to refrain from egg donation for 6 months following ITVISMA injection. Advise men capable of fathering a child to use a barrier method of contraception and to refrain from sperm donation for 3 months following ITVISMA injection [see Use in Specific Populations (8.3)].

Manufactured by, Packed by, Distributed by:

Novartis Gene Therapies, Inc.

2275 Half Day Road

Bannockburn, IL 60015 USA

U.S. License Number 2250

©2025 Novartis Gene Therapies, Inc.

T2025-67

PRINCIPAL DISPLAY PANEL

NDC 71894-200-02

Rx only

onasemnogene
abeparvovec-brve

itvisma®

1.2 × 10^14 vector genomes/ 3 mL

(4 x 10^13 vector genomes (vg)/mL)

Sterile solution for Intrathecal Injection Only

One Single-dose Vial

Must use within 14 days of receipt

DO NOT SHAKE | DO NOT REFREEZE

NOVARTIS